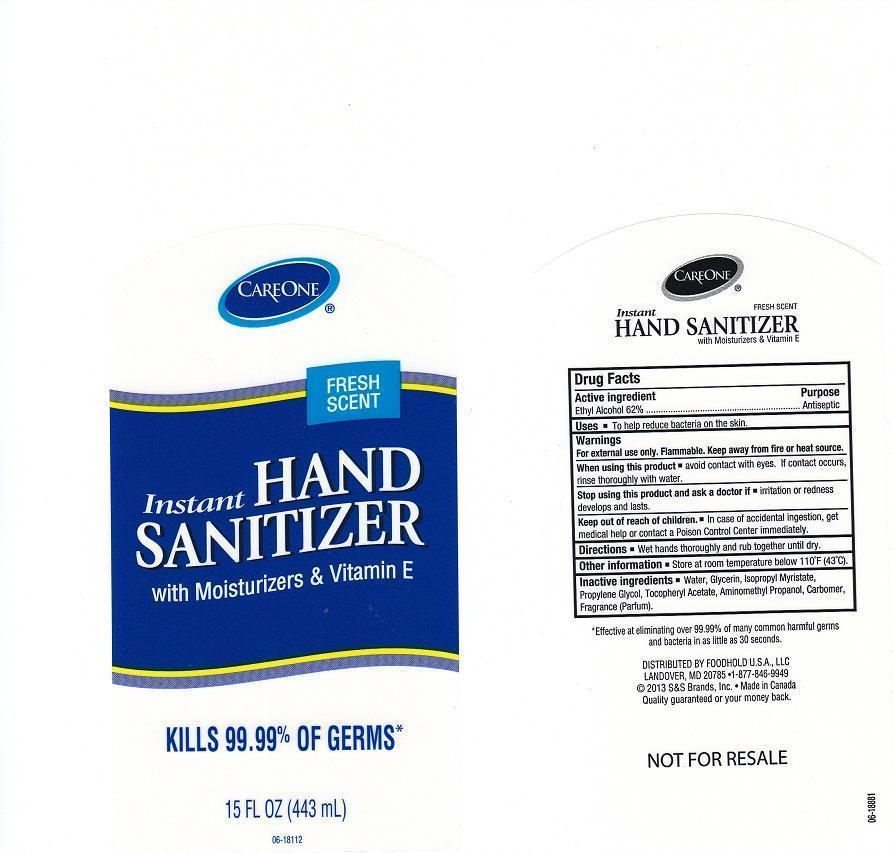 DRUG LABEL: CAREONE
NDC: 41520-220 | Form: LIQUID
Manufacturer: AMERICAN SALES COMPANY
Category: otc | Type: HUMAN OTC DRUG LABEL
Date: 20130607

ACTIVE INGREDIENTS: ALCOHOL 620 mg/1 mL
INACTIVE INGREDIENTS: WATER; GLYCERIN; ISOPROPYL MYRISTATE; PROPYLENE GLYCOL; .ALPHA.-TOCOPHEROL ACETATE; AMINOMETHYLPROPANOL; CARBOMER 934

DRUG FACTS

ACTIVE INGREDIENT

ETHYL ALCOHOL 62%

PURPOSE

ANTISEPTIC

USES

TO HELP REDUCE BACTERIA ON THE SKIN.

WARNINGS

FOR EXTERNAL USE ONLY. FLAMMABLE. KEEP AWAY FROM FIRE OR HEAT SOURCE.

WHEN USING THIS PRODUCT

AVOID CONTACT WITH EYES. IF CONTACT OCCURS, RINSE THOROUGHLY WITH WATER.

STOP USING THIS PRODUCT AND ASK A DOCTOR IF

IRRITATION OR REDNESS DEVELOPS AND LASTS.

KEEP OUT OF REACH OF CHILDREN

IN CASE OF ACCIDENTAL INGESTION, GET MEDICAL HELP OR CONTACT A POISON CONTROL CENTER IMMEDIATELY.

DIRECTIONS

WET HANDS THOROUGHLY AND RUB TOGETHER UNTIL DRY.

OTHER INFORMATION

STORE AT ROOM TEMPERATURE BELOW 110F (43C).

INACTIVE INGREDIENTS

WATER, GLYCERIN, ISOPROPYL MYRISTATE, PROPYLENE GLYCOL, TOCOPHERYL ACETATE, AMINOMETHYL PROPANOL, CARBOMER, FRAGRANCE (PARFUM).